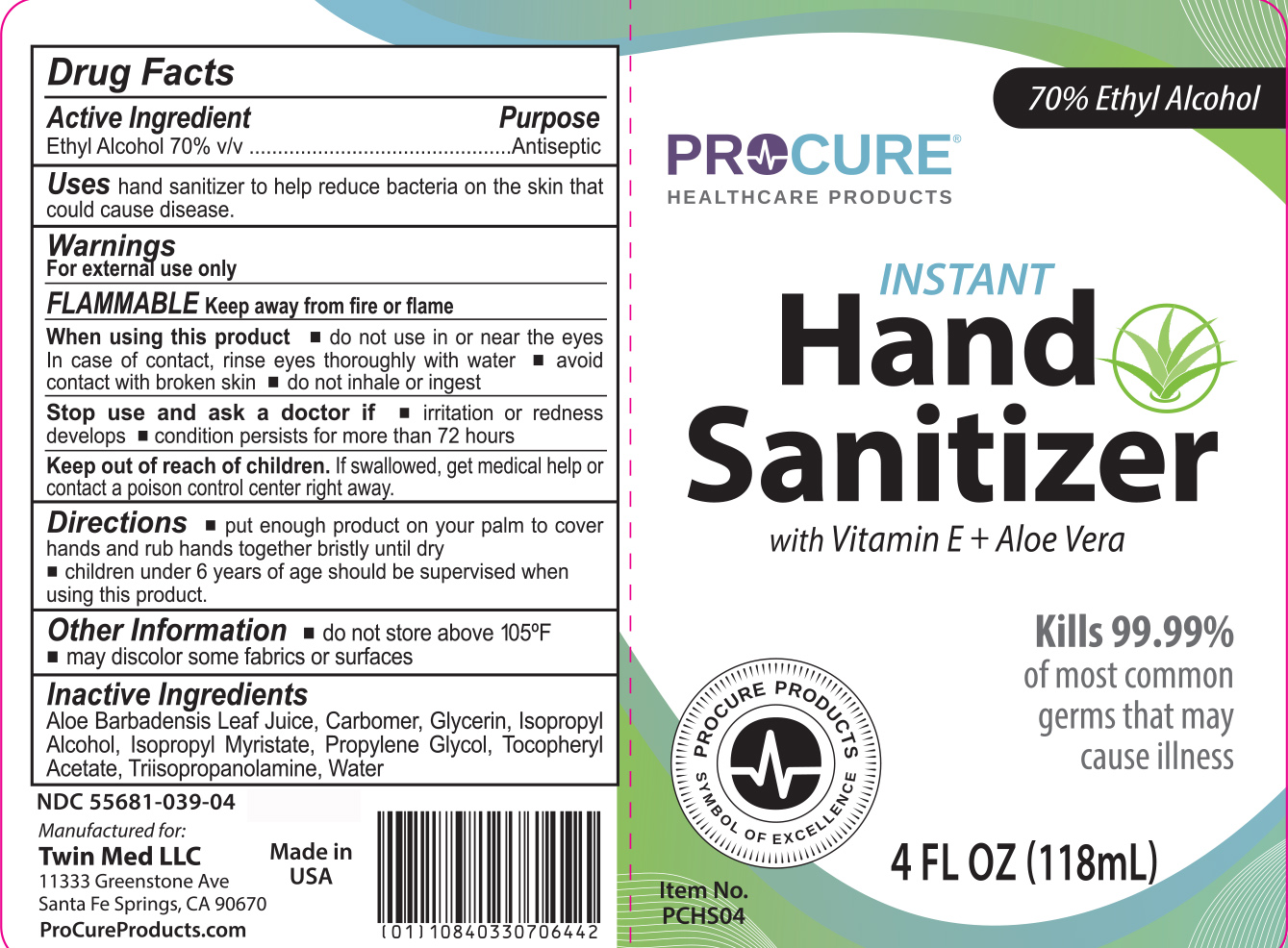 DRUG LABEL: ProCure Hand Sanitizer
NDC: 55681-039 | Form: GEL
Manufacturer: Twin Med LLC
Category: otc | Type: HUMAN OTC DRUG LABEL
Date: 20250829

ACTIVE INGREDIENTS: ALCOHOL 70 mL/100 mL
INACTIVE INGREDIENTS: ISOPROPYL ALCOHOL; PROPYLENE GLYCOL; ALOE BARBADENSIS LEAF JUICE; CARBOMER HOMOPOLYMER, UNSPECIFIED TYPE; TRIISOPROPANOLAMINE; .ALPHA.-TOCOPHEROL ACETATE; WATER; GLYCERIN; ISOPROPYL MYRISTATE

Active Ingredient

Ethyl Alcohol 70% v/v

Purpose

Antiseptic

Uses

Uses hand sanitizer to help reduce bacteria on the skin that could cause disease

Warnings

For external use only

FLAMMABLE. Keep away from fire or flame

When using this product

- do not use in or near the eyes. In case of contact, rinse eyes thoroughly with water
- avoid contact with broken skin
- do not inhale or ingest

Stop use and ask a doctor if

- irritation or redness develops
- condition persists for more than 72 hours

Keep out of reach of children. If swallowed, get medical help or contact a poison control center right away

Directions

- Put enough product on your palm to cover hands and rub hands together bristly until dry
- Children under 6 years of age should be supervised when using this product

Inactive Ingredients

Aloe Barbadensis Leaf Juice, Carbomer, Glycerin, Isopropyl Alcohol, Isopropyl Myristate, Propylene Glycol, Tocopheryl Acetate, Triisopropanolamine, Water